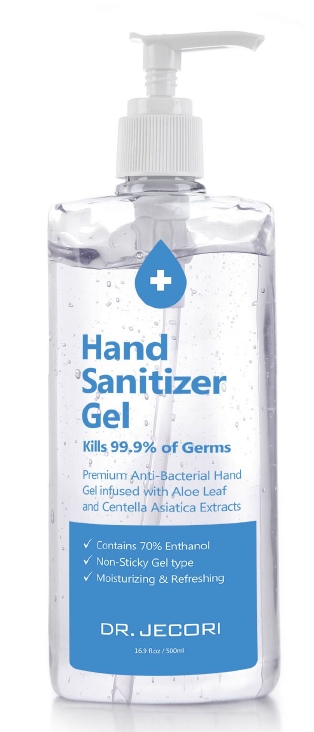 DRUG LABEL: DR.JECORI HAND SANITIZER
NDC: 74921-0001 | Form: GEL
Manufacturer: COSMEDIQUE CO.,LTD.
Category: otc | Type: HUMAN OTC DRUG LABEL
Date: 20200410

ACTIVE INGREDIENTS: ALCOHOL 70 g/100 mL
INACTIVE INGREDIENTS: ALOE; WATER; GLYCERIN

Drug Facts

ACTIVE INGREDIENT

Alcohol

INACTIVE INGREDIENT

Water, Glycerin, Carbomer, etc.

PURPOSE

Antimicrobial

KEEP OUT OF REACH OF THE CHILDREN

INDICATIONS AND USAGE

Store under 30°C (86°F)

WARNINGS

For external use only.

Flammable, keep away from fire or flame.

When using this product keep out of eyes. If contact with eyes occurs, rinse promptly and thoroughly with water.

Stop use and ask a doctor if significant irritation or sensitization develops.

Keep out of reach of children. If swallowed, get medical help or contact a Poison Control Center right away.

DOSAGE AND ADMINISTRATION

1.Place a drop of alcohol based hand sanitizer, the size of a dime in your palm.
2.Rub palm to palm, back of hands, in between fingers and back of fingers, around the thumbs
and tips of fingers for 15-20 seconds
3.Keep rubbing until your hands are dry.